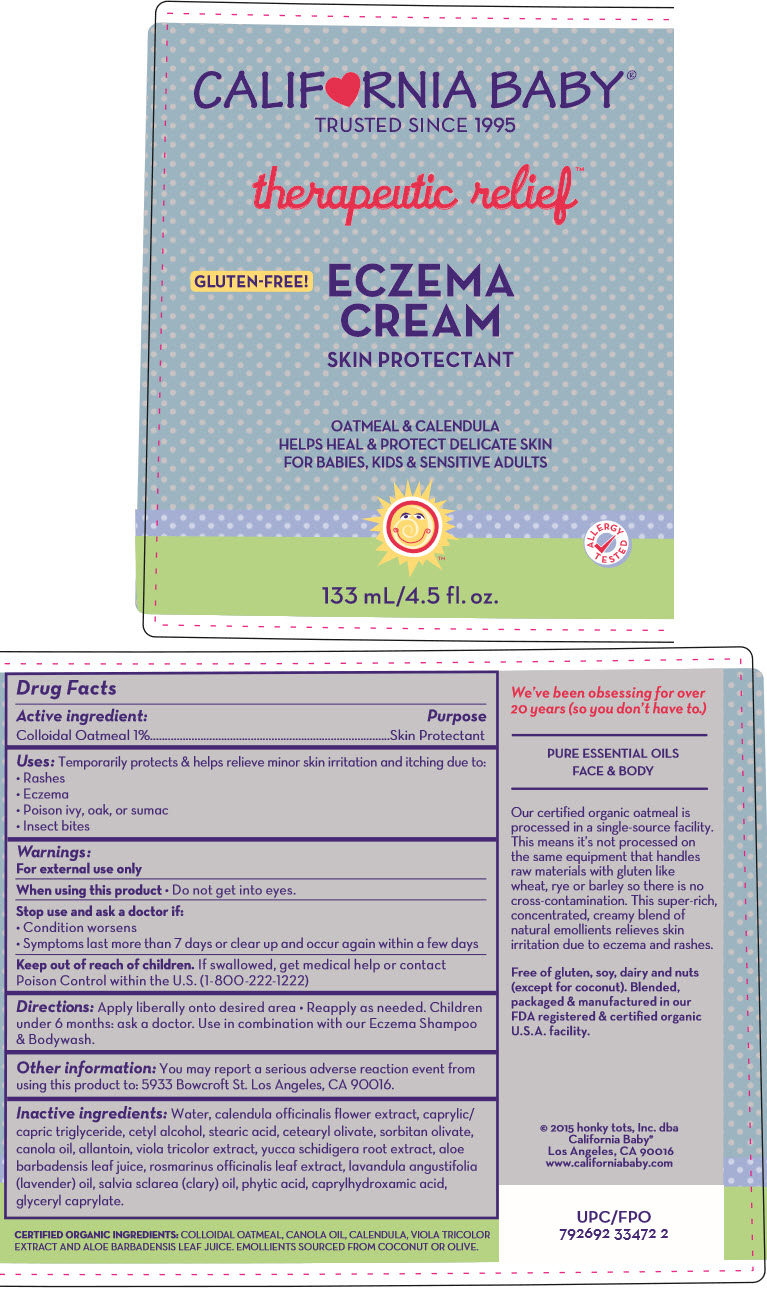 DRUG LABEL: ECZEMA
NDC: 52915-120 | Form: CREAM
Manufacturer: ORGANIC & SUSTAINABLE BEAUTY
Category: otc | Type: HUMAN OTC DRUG LABEL
Date: 20241105

ACTIVE INGREDIENTS: OATMEAL 10 mg/1 mL
INACTIVE INGREDIENTS: Water; medium-chain triglycerides; cetyl alcohol; stearic acid; cetearyl olivate; sorbitan olivate; canola oil; allantoin; calendula officinalis flower; VIOLA TRICOLOR WHOLE; yucca schidigera root; aloe vera leaf; rosemary; lavender oil; clary sage oil; fytic acid; caprylhydroxamic acid; GLYCERYL MONOCAPRYLATE

ECZEMA CREAM

Drug Facts

Active ingredient

Colloidal Oatmeal 1%

Purpose

Skin Protectant

Uses

Temporarily protects & helps relieve minor skin irritation and itching due to:

- Rashes
- Eczema
- Poison ivy, oak, or sumac
- Insect bites

Warnings

For external use only

When using this product

- Do not get into eyes.

Stop use and ask a doctor if

- Condition worsens
- Symptoms last more than 7 days or clear up and occur again within a few days

Keep out of reach of children. If swallowed, get medical help or contact Poison Control within the U.S. (1-800-222-1222)

Directions

Apply liberally onto desired area

- Reapply as needed. Children under 6 months: ask a doctor. Use in combination with our Eczema Shampoo & Bodywash.

Other information

You may report a serious adverse reaction event from using this product to: 5933 Bowcroft St. Los Angeles, CA 90016.

Inactive ingredients

Water, calendula officinalis flower extract, caprylic/capric triglyceride, cetyl alcohol, stearic acid, cetearyl olivate, sorbitan olivate, canola oil, allantoin, viola tricolor extract, yucca schidigera root extract, aloe barbadensis leaf juice, rosmarinus officinalis leaf extract, lavandula angustifolia (lavender) oil, salvia sclarea (clary) oil, phytic acid, caprylhydroxamic acid, glyceryl caprylate.

PRINCIPAL DISPLAY PANEL - 133 mL Container Label

CALIF♥RNIA BABY®
TRUSTED SINCE 1995

therapeutic relief™

GLUTEN-FREE!
ECZEMA
CREAM
SKIN PROTECTANT

OATMEAL & CALENDULA
HELPS HEAL & PROTECT DELICATE SKIN
FOR BABIES, KIDS & SENSITIVE ADULTS

ALLERGY
TESTED

133 mL/4.5 fl. oz.